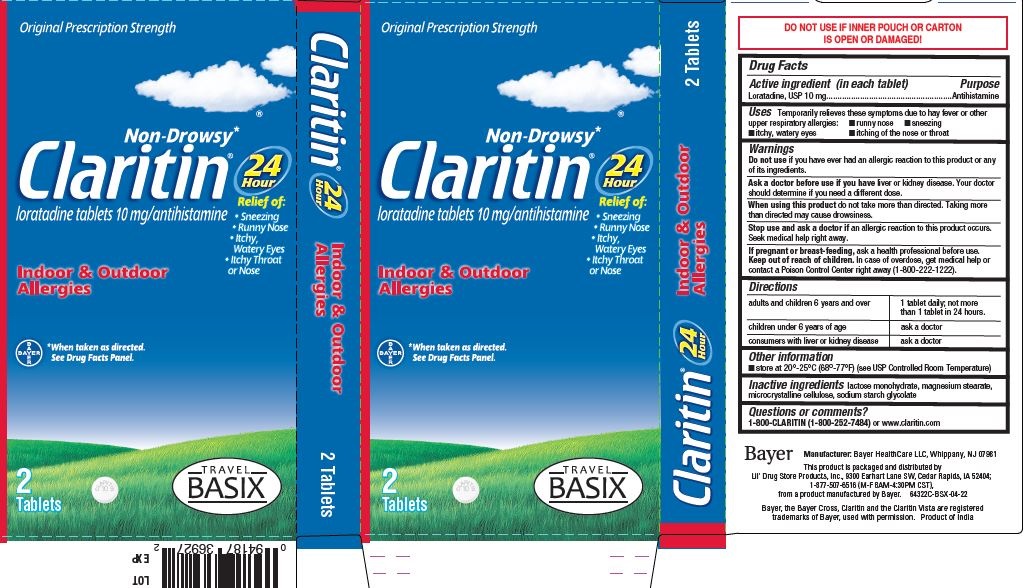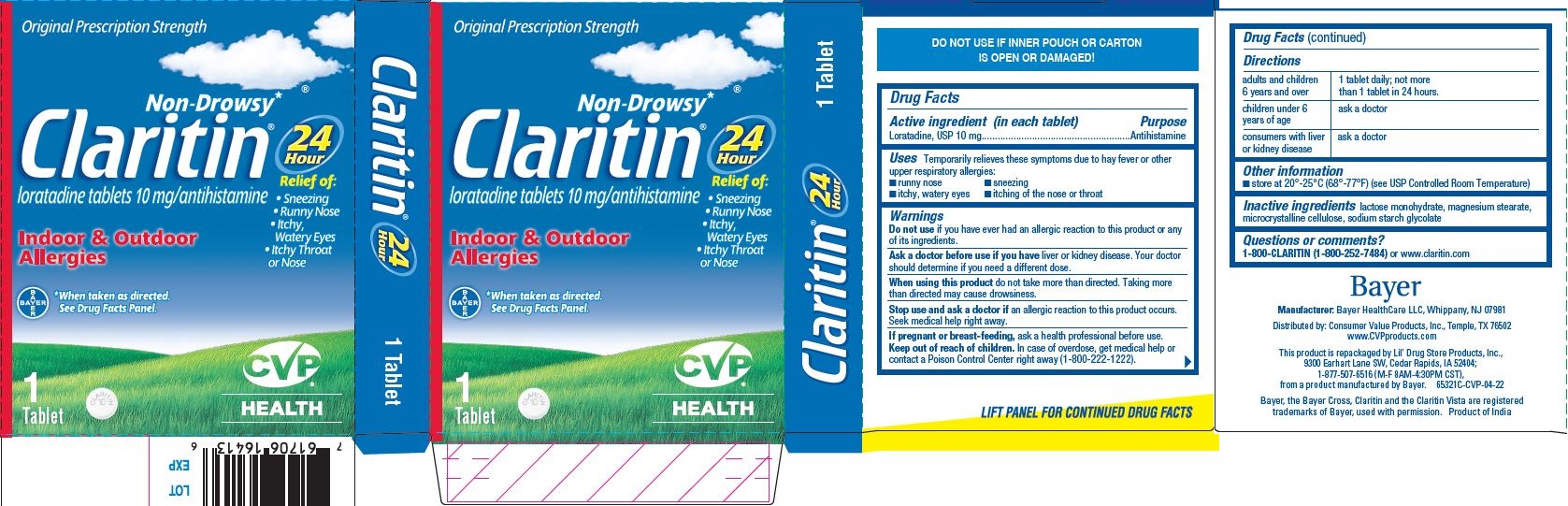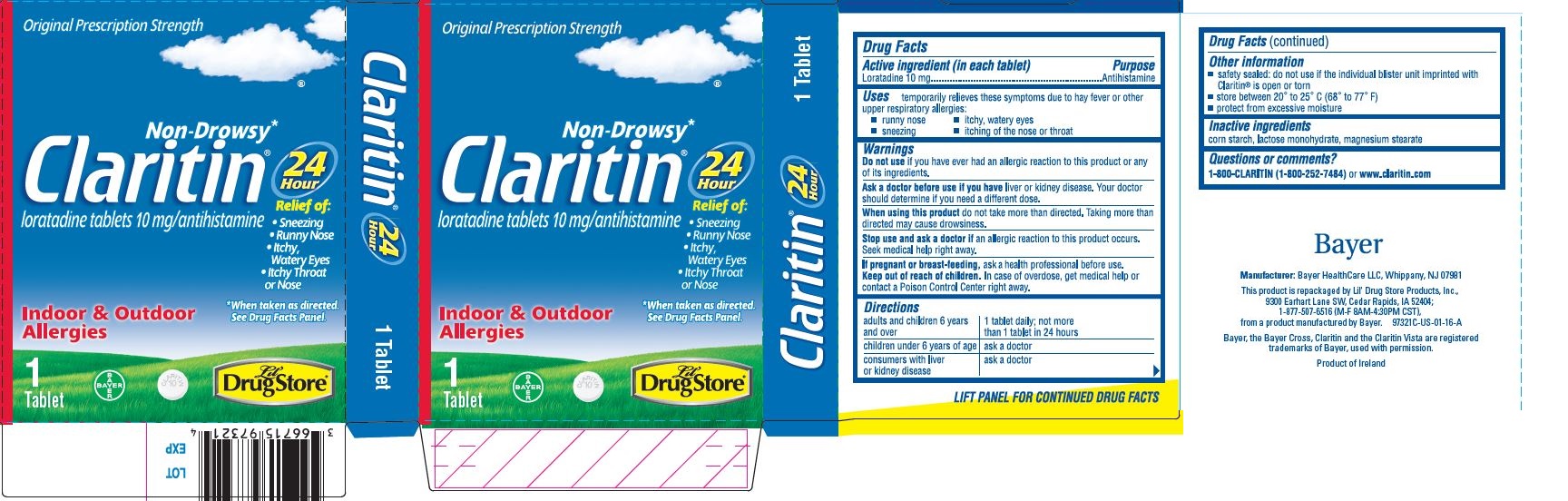 DRUG LABEL: Lil Drug Store Claritin
NDC: 66715-9732 | Form: TABLET
Manufacturer: Lil' Drug Store Products, Inc
Category: otc | Type: HUMAN OTC DRUG LABEL
Date: 20230317

ACTIVE INGREDIENTS: LORATADINE 10 mg/1 1
INACTIVE INGREDIENTS: STARCH, CORN; LACTOSE MONOHYDRATE; MAGNESIUM STEARATE

Claritin®
Antihistamine

Drug Facts

Active ingredient (in each tablet)

Loratadine 10 mg

Purpose

Antihistamine

Uses

temporarily relieves these symptoms due to hay fever or other upper respiratory allergies:

- runny nose
- itchy, watery eyes
- sneezing
- itching of the nose or throat

Warnings

Do not use if you have ever had an allergic reaction to this product or any of its ingredients.

Ask a doctor before use if you have liver or kidney disease. Your doctor should determine if you need a different dose.

When using this product do not take more than directed. Taking more than directed may cause drowsiness.

Stop use and ask a doctor if an allergic reaction to this product occurs. Seek medical help right away.

PREGNANCY OR BREAST FEEDING

If pregnant or breast-feeding, ask a health professional before use.

Keep out of reach of children. In case of overdose, get medical help or contact a Poison Control Center right away.

Directions

adults and children 6 years and over | 1 tablet daily; not more than 1 tablet in 24 hours
children under 6 years of age | ask a doctor
consumers with liver or kidney disease | ask a doctor

Other information

- safety sealed: do not use if the individual blister unit imprinted with Claritin® is open or torn
- store between 20° to 25° C (68° to 77° F)
- protect from excessive moisture

Inactive ingredients

corn starch, lactose monohydrate, magnesium stearate

Questions or comments?

1-800-CLARITIN (1-800-252-7484) or www.claritin.com

PRODUCT MANUFACTURED BY:
MSD CONSUMER CARE, INC.,
P.O. BOX 377, MEMPHIS, TN 38151 USA,
A SUBSIDIARY OF MERCK & CO., INC.,
WHITEHOUSE STATION, NJ USA.

PRINCIPAL DISPLAY PANEL - 1 Tablet Pouch Carton - Lil' Drug Store

Original Prescription Strength

Non-Drowsy* Claritin® loratadine tablets 10 mg/antihistamine

24 Hour

Relief of:

- Sneezing
- Runny Nose
- Itchy,

Watery Eyes

- Itchy Throat

or Nose

*When taken as directed. See Drug Facts Panel.

Indoor & Outdoor Allergies

1 Tablet

Principal Display Panel/Package - BSX

Original Prescription Strength

Non-Drowsy* Claritin® loratadine tablets 10 mg/antihistamine

24 Hour

Relief of:

- Sneezing
- Runny Nose
- Itchy,

Watery Eyes

- Itchy Throat

or Nose

Indoor & Outdoor Allergies

[Bayer cross]* When taken as directed.

See Drug Facts Panel.

1 Tablet

[tablet image]

TRAVEL

BASIX

Principal Display Panel - CVP

Original Prescription Strength

Non-Drowsy* Claritin® loratadine tablets 10 mg/antihistamine

24 Hour

Relief of:

Sneezing Runny Nose Itchy,

Watery Eyes

Itchy Throat

or Nose

Indoor & Outdoor Allergies

[Bayer cross]*When taken as directed. See Drug Facts Panel.

1 Tablet

[tablet image]

CVP

HEALTH